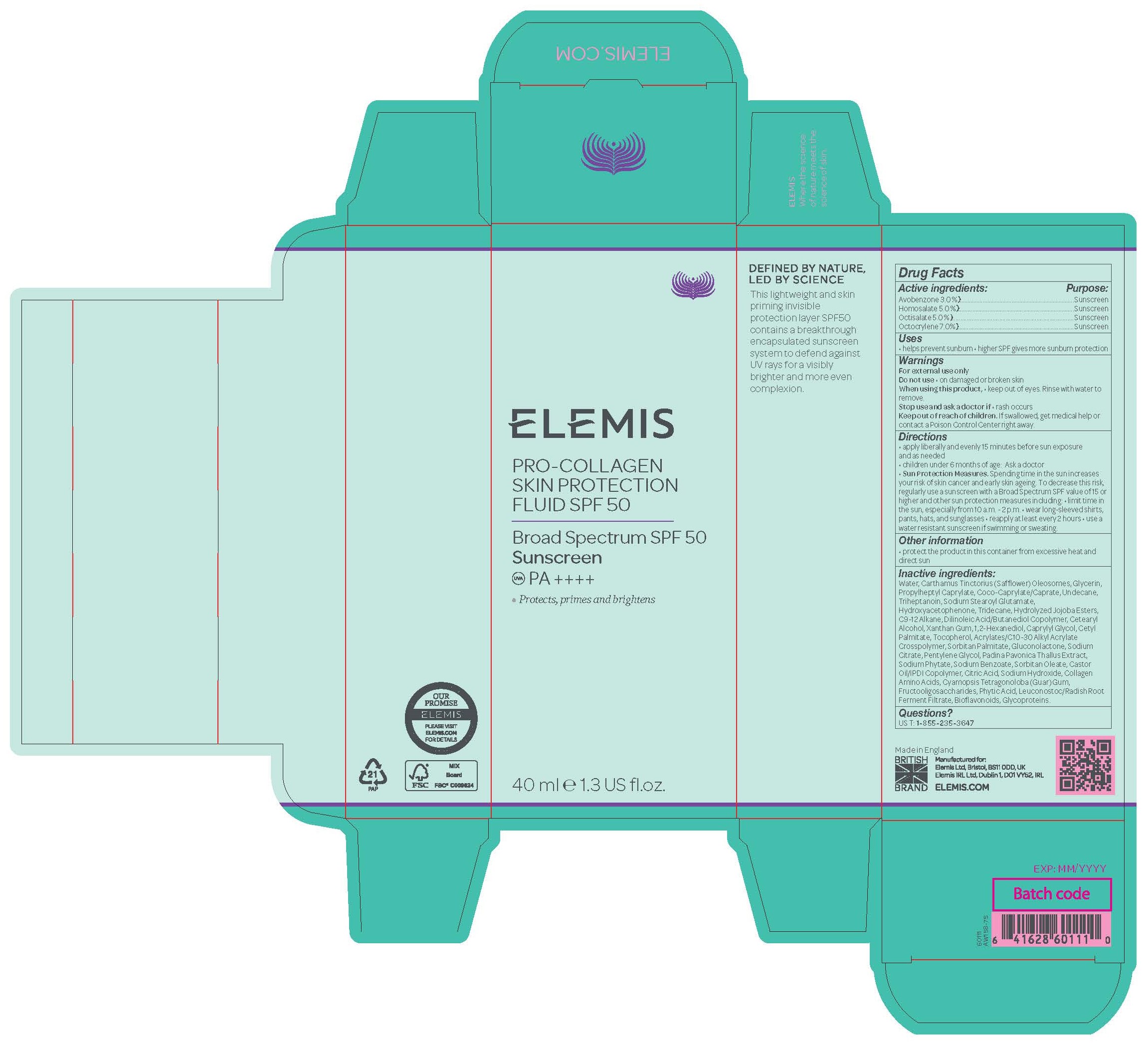 DRUG LABEL: PRO-COLLAGEN SKIN PROTECTION FLUID SPF 50
NDC: 65912-012 | Form: CREAM
Manufacturer: Elemis Ltd.
Category: otc | Type: HUMAN OTC DRUG LABEL
Date: 20251120

ACTIVE INGREDIENTS: AVOBENZONE 3 mg/100 g; HOMOSALATE 5 mg/100 g; OCTISALATE 5 mg/100 g; OCTOCRYLENE 7 mg/100 g
INACTIVE INGREDIENTS: GLYCERIN; HYDROLYZED JOJOBA ESTERS (ACID FORM); DILINOLEIC ACID/BUTANEDIOL COPOLYMER; CASTOR OIL/IPDI COPOLYMER; TRIHEPTANOIN; PENTYLENE GLYCOL; HYDROXYACETOPHENONE; C9-12 ALKANE; CETOSTEARYL ALCOHOL; 1,2-HEXANEDIOL; SODIUM STEAROYL GLUTAMATE; SORBITAN MONOPALMITATE; SODIUM CITRATE; UNDECANE; SODIUM HYDROXIDE; TOCOPHEROL; SORBITAN MONOOLEATE; XANTHAN GUM; CAPRYLYL GLYCOL; ACRYLATES/C10-30 ALKYL ACRYLATE CROSSPOLYMER (60000 MPA.S); GLUCONOLACTONE; GUAR GUM; CETYL PALMITATE; CARTHAMUS TINCTORIUS (SAFFLOWER) OLEOSOMES; PROPYLHEPTYL CAPRYLATE; COCO-CAPRYLATE/CAPRATE; TRIDECANE; SODIUM BENZOATE; HYDROLYZED SOY PROTEIN (ENZYMATIC; 2000 MW); WATER; CITRIC ACID MONOHYDRATE; FYTIC ACID; LEUCONOSTOC/RADISH ROOT FERMENT FILTRATE; PHYTATE SODIUM; PADINA PAVONICA; HYDROLYZED CORN PROTEIN (ENZYMATIC; 1500 MW); HYDROLYZED WHEAT PROTEIN (ENZYMATIC, 3000 MW)

PRO-COLLAGEN SKIN PROTECTION FLUID SPF 50

Drug Facts

ACTIVE INGREDIENT

Avobenzone 3.0 %

Homosalate 5.0 %

Octisalate 5.0 %

Octocrylene 7.0%

PURPOSE

Sunscreen

INDICATIONS AND USAGE

• helps prevent sunburn

• higher SPF gives more sunburn protection

WARNINGS

For external use only

DO NOT USE

• on damaged or broken skin

WHEN USING

• keep out of eyes. Rinse with water to remove.

STOP USE

• rash occurs

Keep out of reach of children. If swallowed, get medical help or contact a Poison Control Center right away.

DOSAGE AND ADMINISTRATION

• apply liberally and evenly 15 minutes before sun exposure and as needed
• children under 6 months of age: Ask a doctor
• Sun Protection Measures. Spending time in the sun increases your risk of skin cancer and early skin ageing. To decrease this risk,
regularly use a sunscreen with a Broad Spectrum SPF value of 15 or higher and other sun protection measures including:

• limit time in the sun, especially from 10 a.m. - 2 p.m.

• wear long-sleeved shirts, pants, hats, and sunglasses

• reapply at least every 2 hours

• use a water resistant sunscreen if swimming or sweating.

STORAGE AND HANDLING

• protect the product in this container from excessive heat and direct sun

INACTIVE INGREDIENT

Water, Carthamus Tinctorius (Safflower) Oleosomes, Glycerin, Propylheptyl Caprylate, Coco-Caprylate/Caprate, Undecane, Triheptanoin, Sodium Stearoyl Glutamate, Hydroxyacetophenone, Tridecane, Hydrolyzed Jojoba Esters, C9-12 Alkane, Dilinoleic Acid/Butanediol Copolymer, Cetearyl Alcohol, Xanthan Gum, 1,2-Hexanediol, Caprylyl Glycol, Cetyl Palmitate, Tocopherol, Acrylates/C10-30 Alkyl Acrylate Crosspolymer, Sorbitan Palmitate, Gluconolactone, Sodium Citrate, Pentylene Glycol, Padina Pavonica Thallus Extract, Sodium Phytate, Sodium Benzoate, Sorbitan Oleate, Castor Oil/IPDI Copolymer, Citric Acid, Sodium Hydroxide, Collagen Amino Acids, Cyamopsis Tetragonoloba (Guar) Gum, Fructooligosaccharides, Phytic Acid, Leuconostoc/Radish Root Ferment Filtrate, Bioflavonoids, Glycoproteins.

QUESTIONS

US T: 1-855-235-3647

PACKAGE LABEL

Pro-Collagen Skin Protection Fluid SPF 50

Broad Spectrum SPF 50 Sunscreen

Protects, primes and brightens

40 ml e 1.3 US fl.oz.